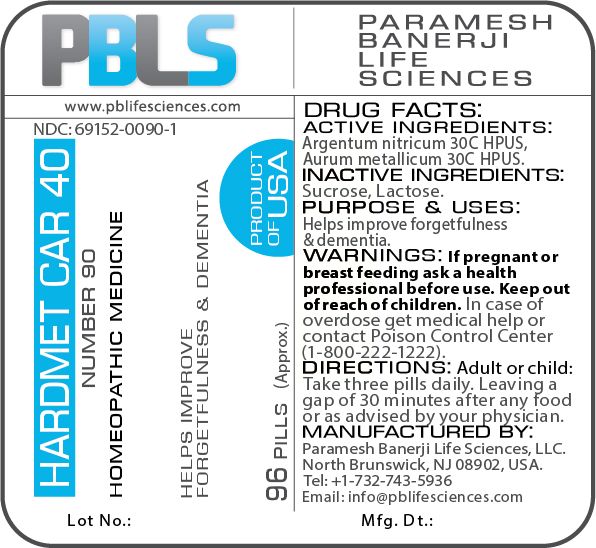 DRUG LABEL: Hardmet Car 40 (Number 90)
NDC: 69152-0090 | Form: PELLET
Manufacturer: Paramesh Banerji Life Sciences LLC
Category: homeopathic | Type: HUMAN OTC DRUG LABEL
Date: 20180702

ACTIVE INGREDIENTS: SILVER NITRATE 30 [hp_C]/1 1; GOLD 30 [hp_C]/1 1
INACTIVE INGREDIENTS: SUCROSE; LACTOSE

DRUG FACTS: Active Ingredients

Argentum nitricum 30C HPUS, Aurum metallicum 30C HPUS

Inactive Ingredients

Sucrose, Lactose

Purpose

Helps improve forgetfulness and dementia

Uses

Helps improve forgetfulness and dementia

Warnings

If pregnant or breast feeding ask a health professional before use.

Keep out of reach of children. In case of overdose, get medical help or contact a Poison Control Center (1-800-222-1222) right away.

Direction

Adult or child: Take three pills daily. Leaving a gap of 30 minutes after any food or as advised by your physician.

Manufactured by

Paramesh Banerji Life Sciences, LLC.

North Brunswick, NJ 08902, USA.

Tel: +1-732-743-5936

Email: info@pblifesciences.com

Principal Display Panel

NDC: 69152-0090-1

Hardmet Car 40

Number 90

Homeopathic Medicine

Helps improve forgetfulness and dementia

96 Pills (Approx.)

Product of USA